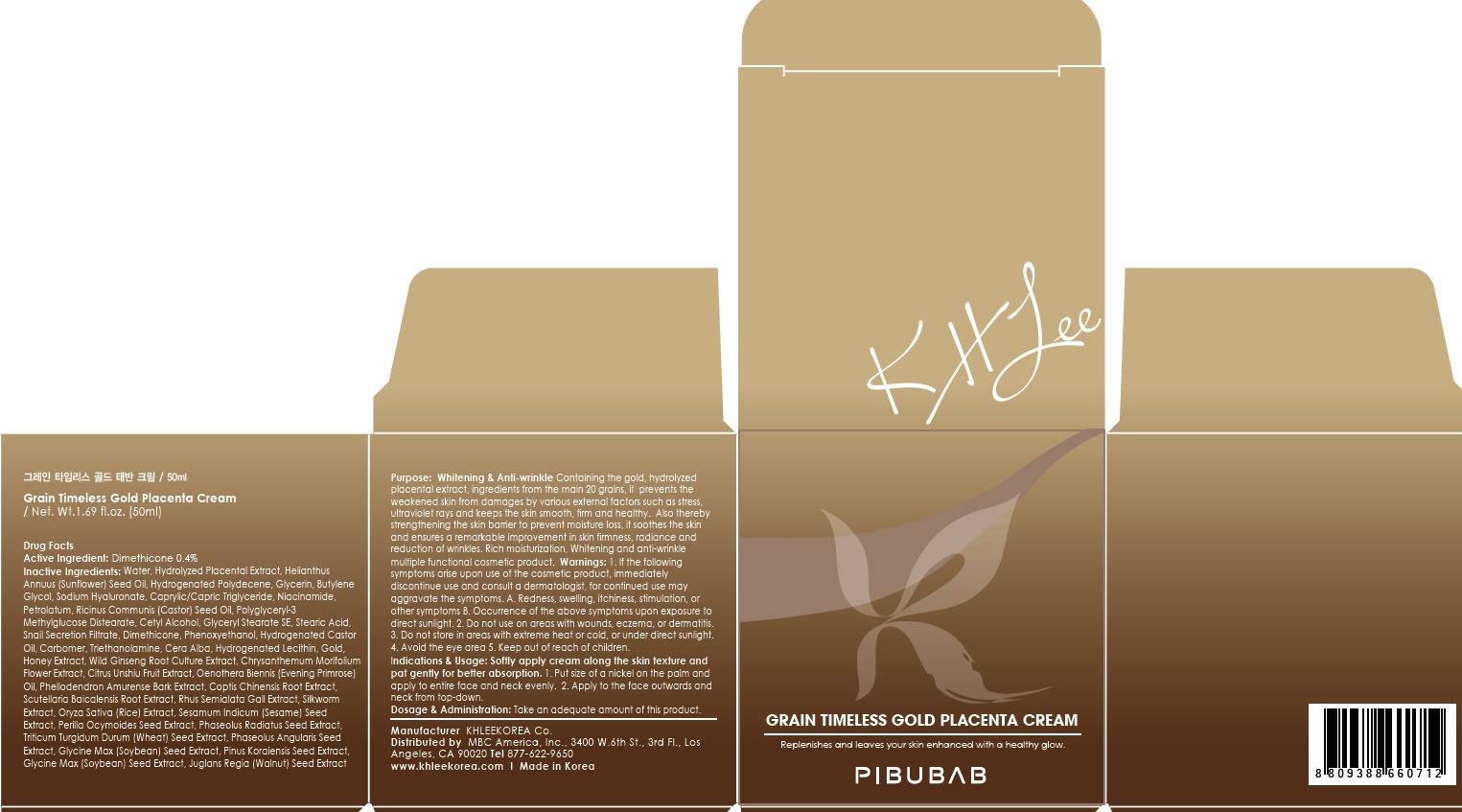 DRUG LABEL: Grain Timeless Gold Placenta
NDC: 70567-050 | Form: CREAM
Manufacturer: KHLEEKOREA
Category: otc | Type: HUMAN OTC DRUG LABEL
Date: 20160418

ACTIVE INGREDIENTS: Dimethicone 0.2 g/50 mL
INACTIVE INGREDIENTS: Water; Glycerin

ACTIVE INGREDIENT

Active Ingredient: Dimethicone 0.4%

INACTIVE INGREDIENT

Inactive Ingredients: Water, Hydrolyzed Placental Extract, Helianthus Annuus (Sunflower) Seed Oil, Hydrogenated Polydecene, Glycerin, Butylene Glycol, Sodium Hyaluronate, Caprylic/Capric Triglyceride, Niacinamide, Petrolatum, Ricinus Communis (Castor) Seed Oil, Polyglyceryl-3 Methylglucose Distearate, Cetyl Alcohol, Glyceryl Stearate SE, Stearic Acid, Snail Secretion Filtrate, Phenoxyethanol, Hydrogenated Castor Oil, Carbomer, Triethanolamine, Cera Alba, Hydrogenated Lecithin, Gold, Honey Extract, Wild Ginseng Root Culture Extract, Chrysanthemum Morifolium Flower Extract, Citrus Unshiu Fruit Extract, Oenothera Biennis (Evening Primrose) Oil, Phellodendron Amurense Bark Extract, Coptis Chinensis Root Extract, Scutellaria Baicalensis Root Extract, Rhus Semialata Gall Extract, Silkworm Extract, Oryza Sativa (Rice) Extract, Sesamum Indicum (Sesame) Seed Extract, Perilla Ocymoides Seed Extract, Phaseolus Radiatus Seed Extract, Triticum Turgidum Durum (Wheat) Seed Extract, Phaseolus Angularis Seed Extract, Glycine Max (Soybean) Seed Extract, Pinus Koraiensis Seed Extract, Glycine Max (Soybean) Seed Extract, Juglans Regia (Walnut) Seed Extract

PURPOSE

Purpose: Whitening & Anti-wrinkle

Containing the gold, hydrolyzed placental extract, ingredients from the main 20 grains, it prevents the weakened skin from damages by various external factors such as stress, ultraviolet rays and keeps the skin smooth, firm and healthy. Also thereby strengthening the skin barrier to prevent moisture loss, it soothes the skin and ensures a remarkable improvement in skin firmness, radiance and reduction of wrinkles. Rich moisturization, Whitening and anti-wrinkle multiple functional cosmetic product.

WARNINGS

Warnings: 1. If the following symptoms arise upon use of the cosmetic product, immediately discontinue use and consult a dermatologist, for continued use may aggravate the symptoms. A. Redness, swelling, itchiness, stimulation, or other symptoms B. Occurrence of the above symptoms upon exposure to direct sunlight. 2. Do not use on areas with wounds, eczema, or dermatitis. 3. Do not store in areas with extreme heat or cold, or under direct sunlight. 4. Avoid the eye area 5. Keep out of reach of children

KEEP OUT OF REACH OF CHILDREN

INDICATIONS & USAGE

Indications & Usage: Softly apply cream along the skin texture and pat gently for better absorption. 1. Put size of a nickel on the palm and apply to entire face and neck evenly. 2. Apply to the face outwards and neck from top-down.

DOSAGE & ADMINISTRATION

Dosage & Administration: Take an adequate amount of this product.